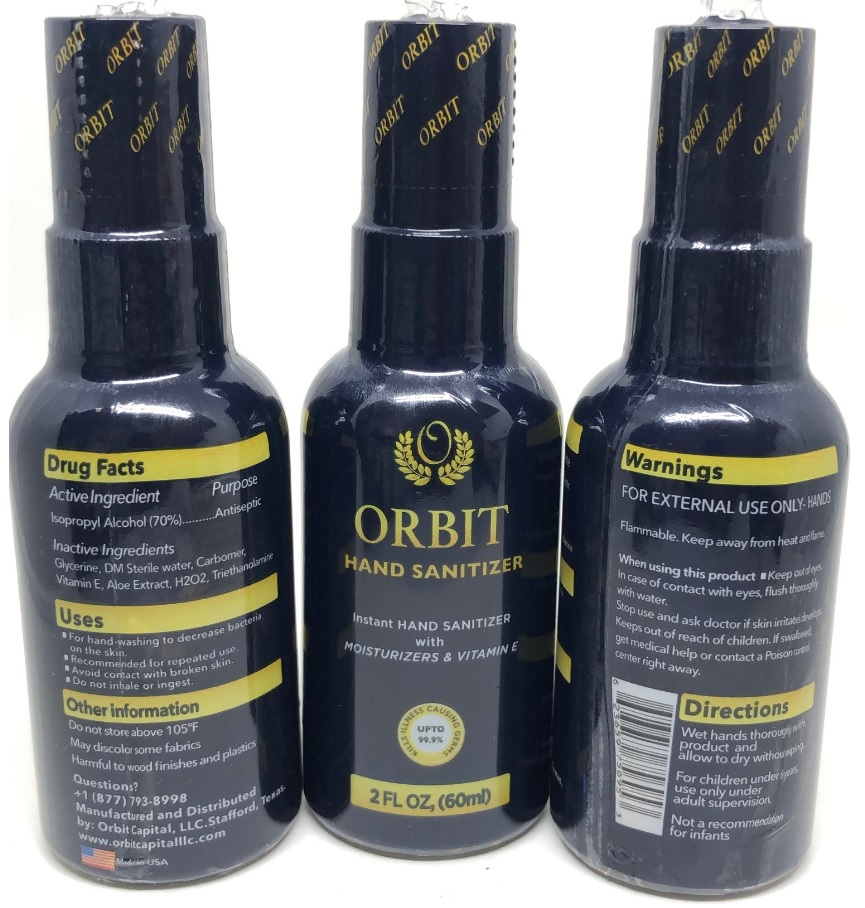 DRUG LABEL: Orbit Hand Sanitizer
NDC: 78752-698 | Form: SPRAY
Manufacturer: ORBIT CAPITAL LLC
Category: otc | Type: HUMAN OTC DRUG LABEL
Date: 20200827

ACTIVE INGREDIENTS: ISOPROPYL ALCOHOL 70 mL/100 mL
INACTIVE INGREDIENTS: GLYCERIN; WATER; CARBOMER HOMOPOLYMER, UNSPECIFIED TYPE; .ALPHA.-TOCOPHEROL; ALOE; HYDROGEN PEROXIDE; TROLAMINE

ORBIT HAND SANITIZER

Active Ingredient

Isopropyl Alcohol (70%)

Purpose

Antiseptic

Inactive Ingredients

Glycerine, DM Sterile water, Carbomer, Vitamin E, Aloe Extract, H2O2, Triethanolamine

Uses

▪ For hand-washing to decrease bacteria on the skin.

▪ Recommended for repeated use.

▪ Avoid contact with broken skin.

▪ Do not inhale or ingest.

Other information

Do not store above 105°F

May discolor some fabrics

Harmful to wood finishes and plastics

Questions?

+1(877)793-8998

Warnings

FOR EXTERNAL USE ONLY - HANDS

Flammable. Keep away from heat and flame.

When using this product • Keep out of eyes. In case of contact with eyes, flush thoroughly with water.

Stop use and ask a doctor if skin irritates develops.

KEEP OUT OF REACH OF CHILDREN

Keeps out of reach of children. If swallowed, get medical help or contact a Poison control center right away.

Directions

Wet hands thoroughly with product and allow to dry without wiping.

For children under 6 years, use only under adult supervision.

Not a recommendation for infants

Instant HAND SANITIZER with MOISTURIZERS & VITAMIN E

KILLS ILLNESS CAUSING GERMS UPTO 99.9%

Manufactured and Distributed

by: Orbit Capital, LLC.Stafford, Texas.

www.orbitcapitalllc.com

Made in USA